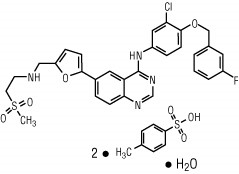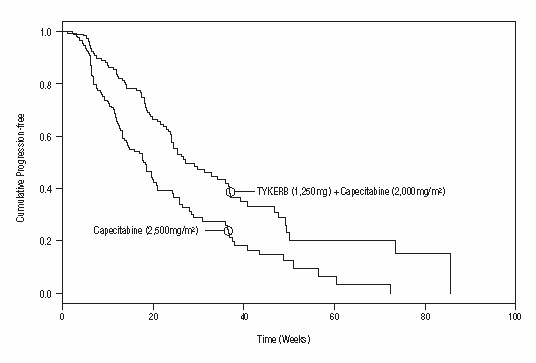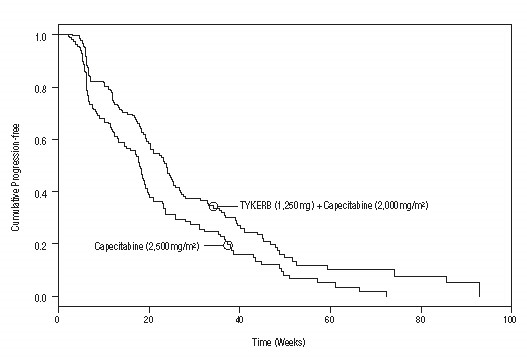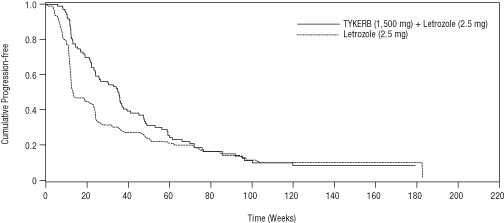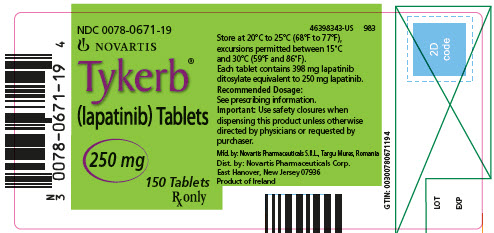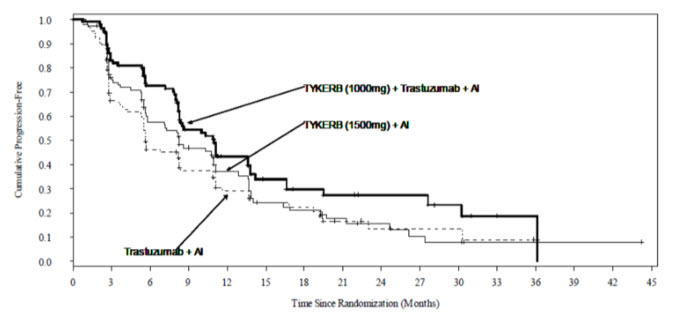 DRUG LABEL: TYKERB
NDC: 0078-0671 | Form: TABLET
Manufacturer: Novartis Pharmaceuticals Corporation
Category: prescription | Type: HUMAN PRESCRIPTION DRUG LABEL
Date: 20260127

ACTIVE INGREDIENTS: LAPATINIB DITOSYLATE 250 mg/1 1
INACTIVE INGREDIENTS: MAGNESIUM STEARATE; CELLULOSE, MICROCRYSTALLINE; POVIDONE; SODIUM STARCH GLYCOLATE TYPE A POTATO; FD&C YELLOW NO. 6; HYPROMELLOSES; POLYETHYLENE GLYCOL; POLYSORBATE 80; TITANIUM DIOXIDE

HIGHLIGHTS OF PRESCRIBING INFORMATION

These highlights do not include all the information needed to use TYKERB safely and effectively. See full prescribing information for TYKERB.
TYKERB® (lapatinib) tablets, for oral use
Initial U.S. Approval: 2007

WARNING: HEPATOTOXICITY

See full prescribing information for complete boxed warning.

Hepatotoxicity has been observed in clinical trials and postmarketing experience. The hepatotoxicity may be severe and deaths have been reported. Causality of the deaths is uncertain. (5.2)

1 INDICATIONS AND USAGE

TYKERB is a kinase inhibitor indicated in combination with: (1)

- capecitabine for the treatment of patients with advanced or metastatic breast cancer whose tumors overexpress human epidermal growth factor receptor 2 (HER2) and who have received prior therapy, including an anthracycline, a taxane, and trastuzumab.
  Limitations of Use: Patients should have disease progression on trastuzumab prior to initiation of treatment with TYKERB in combination with capecitabine.
- letrozole for the treatment of postmenopausal women with hormone receptor-positive metastatic breast cancer that overexpresses the HER2 receptor for whom hormonal therapy is indicated.

TYKERB in combination with an aromatase inhibitor has not been compared to a trastuzumab-containing chemotherapy regimen for the treatment of metastatic breast cancer.

2 DOSAGE AND ADMINISTRATION

The recommended dosage of TYKERB for advanced or metastatic breast cancer is 1,250 mg (5 tablets) given orally once daily on Days 1-21 continuously in combination with capecitabine 2,000 mg/m^2/day (administered orally in 2 doses approximately 12 hours apart) on Days 1-14 in a repeating 21-day cycle. (2.1)

The recommended dose of TYKERB for hormone receptor-positive, HER2-positive metastatic breast cancer is 1,500 mg (6 tablets) given orally once daily continuously in combination with letrozole. When TYKERB is coadministered with letrozole, the recommended dose of letrozole is 2.5 mg once daily. (2.1)

- TYKERB should be taken at least one hour before or one hour after a meal. However, capecitabine should be taken with food or within 30 minutes after food. (2.1)
- TYKERB should be taken once daily. Do not divide daily doses of TYKERB. (2.1, 12.3)
- Modify dose for cardiac and other toxicities, severe hepatic impairment, diarrhea, and CYP3A4 drug interactions. (2.2)

3 DOSAGE FORMS AND STRENGTHS

250 mg tablets (3)

4 CONTRAINDICATIONS

Known severe hypersensitivity (e.g., anaphylaxis) to this product or any of its components. (4)

5 WARNINGS AND PRECAUTIONS

- Decreases in left ventricular ejection fraction (LVEF) have been reported. Confirm normal LVEF before starting TYKERB and continue evaluations during treatment. (5.1)
- TYKERB has been associated with hepatotoxicity. Monitor liver function tests before initiation of treatment, every 4 to 6 weeks during treatment, and as clinically indicated. Discontinue and do not restart TYKERB if patients experience severe changes in liver function tests. (5.2)
- Dose reduction in patients with severe hepatic impairment should be considered. (2.2, 5.3, 8.7)
- Diarrhea, including severe diarrhea, has been reported during treatment. Manage with antidiarrheal agents, and replace fluids and electrolytes if severe. (5.4)
- TYKERB has been associated with interstitial lung disease (ILD) and pneumonitis. Discontinue TYKERB if patients experience severe pulmonary symptoms. (5.5)
- TYKERB may prolong the QT interval in some patients. Consider electrocardiogram (ECG) and electrolyte monitoring. (5.6, 12.2)
- Severe cutaneous reactions have been reported. Discontinue TYKERB if life-threatening reactions are suspected. (5.7)
- TYKERB can cause fetal harm. Advise patients of the potential risk to the fetus and to use effective contraception. (5.8, 8.1, 8.3)

6 ADVERSE REACTIONS

The most common (greater than 20%) adverse reactions during treatment with TYKERB plus capecitabine were diarrhea, palmar-plantar erythrodysesthesia, nausea, rash, vomiting, and fatigue. The most common (greater than or equal to 20%) adverse reactions during treatment with TYKERB plus letrozole were diarrhea, rash, nausea, and fatigue. (6.1)

To report SUSPECTED ADVERSE REACTIONS, contact Novartis Pharmaceuticals Corporation at 1-888-669-6682 or FDA at 1-800-FDA-1088 or www.fda.gov/medwatch.

7 DRUG INTERACTIONS

- TYKERB is likely to increase exposure to concomitantly administered drugs which are substrates of CYP3A4, CYP2C8, or P-glycoprotein (ABCB1). (7.1)
- Avoid strong CYP3A4 inhibitors. If unavoidable, consider dose reduction of TYKERB in patients coadministered a strong CYP3A4 inhibitor. (2.2, 7.2)
- Avoid strong CYP3A4 inducers. If unavoidable, consider gradual dose increase of TYKERB in patients coadministered a strong CYP3A4 inducer. (2.2, 7.2)

8 USE IN SPECIFIC POPULATIONS

- Lactation: Advise not to breastfeed. (8.2)
- Females and Males of Reproductive Potential: Verify the pregnancy status of females prior to initiation of TYKERB. (8.3)

FULL PRESCRIBING INFORMATION

WARNING: HEPATOTOXICITY

Hepatotoxicity has been observed in clinical trials and postmarketing experience. The hepatotoxicity may be severe and deaths have been reported. Causality of the deaths is uncertain [see Warnings and Precautions (5.2)].

1 INDICATIONS AND USAGE

TYKERB® is indicated in combination with:

- capecitabine for the treatment of patients with advanced or metastatic breast cancer whose tumors overexpress human epidermal growth factor receptor 2 (HER2) and who have received prior therapy, including an anthracycline, a taxane, and trastuzumab.
  Limitations of Use: Patients should have disease progression on trastuzumab prior to initiation of treatment with TYKERB in combination with capecitabine.
- letrozole for the treatment of postmenopausal women with hormone receptor-positive metastatic breast cancer that overexpresses the HER2 receptor for whom hormonal therapy is indicated.

TYKERB in combination with an aromatase inhibitor has not been compared to a trastuzumab-containing chemotherapy regimen for the treatment of metastatic breast cancer.

2 DOSAGE AND ADMINISTRATION

2.1 Recommended Dosing

HER2-Positive Metastatic Breast Cancer: The recommended dose of TYKERB is 1,250 mg given orally once daily on Days 1-21 continuously in combination with capecitabine 2,000 mg/m^2/day (administered orally in 2 doses approximately 12 hours apart) on Days 1-14 in a repeating 21-day cycle. TYKERB should be taken at least one hour before or one hour after a meal. The dose of TYKERB should be once daily (5 tablets administered all at once); dividing the daily dose is not recommended [see Clinical Pharmacology (12.3)]. Capecitabine should be taken with food or within 30 minutes after food. If a day’s dose is missed, the patient should not double the dose the next day. Treatment should be continued until disease progression or unacceptable toxicity occurs.

Hormone Receptor-Positive, HER2-Positive Metastatic Breast Cancer: The recommended dose of TYKERB is 1,500 mg given orally once daily continuously in combination with letrozole. When coadministered with TYKERB, the recommended dose of letrozole is 2.5 mg once daily. TYKERB should be taken at least one hour before or one hour after a meal. The dose of TYKERB should be once daily (6 tablets administered all at once); dividing the daily dose is not recommended [see Clinical Pharmacology (12.3)].

2.2 Dose Modification Guidelines

Cardiac Events: TYKERB should be discontinued in patients with a decreased left ventricular ejection fraction (LVEF) that is Grade 2 or greater by National Cancer Institute Common Terminology Criteria for Adverse Events (NCI CTCAE v3.0), and in patients with an LVEF that drops below the institution’s lower limit of normal (LLN) [see Warnings and Precautions (5.1) and Adverse Reactions (6.1)]. TYKERB in combination with capecitabine may be restarted at a reduced dose (1,000 mg/day) and in combination with letrozole may be restarted at a reduced dose of 1,250 mg/day after a minimum of 2 weeks if the LVEF recovers to normal and the patient is asymptomatic.

Hepatic Impairment: Patients with severe hepatic impairment (Child-Pugh Class C) should have their dose of TYKERB reduced. A dose reduction from 1,250 mg/day to 750 mg/day (HER2-positive metastatic breast cancer indication) or from 1,500 mg/day to 1,000 mg/day (hormone receptor-positive, HER2-positive breast cancer indication) in patients with severe hepatic impairment is predicted to adjust the area under the curve (AUC) to the normal range and should be considered. However, there are no clinical data with this dose adjustment in patients with severe hepatic impairment.

Diarrhea: TYKERB should be interrupted in patients with diarrhea which is NCI CTCAE Grade 3 or Grade 1 or 2 with complicating features (moderate to severe abdominal cramping, nausea or vomiting greater than or equal to NCI CTCAE Grade 2, decreased performance status, fever, sepsis, neutropenia, frank bleeding, or dehydration). TYKERB may be reintroduced at a lower dose (reduced from 1,250 mg/day to 1,000 mg/day or from 1,500 mg/day to 1,250 mg/day) when diarrhea resolves to Grade 1 or less. TYKERB should be permanently discontinued in patients with diarrhea, which is NCI CTCAE Grade 4 [see Warnings and Precautions (5.4) and Adverse Reactions (6.1)].

Concomitant Strong CYP3A4 Inhibitors: The concomitant use of strong CYP3A4 inhibitors should be avoided (e.g., ketoconazole, itraconazole, clarithromycin, atazanavir, indinavir, nefazodone, nelfinavir, ritonavir, saquinavir, telithromycin, voriconazole). Grapefruit may also increase plasma concentrations of lapatinib and should be avoided. If patients must be coadministered a strong CYP3A4 inhibitor, based on pharmacokinetic studies, a dose reduction to 500 mg/day of lapatinib is predicted to adjust the lapatinib AUC to the range observed without inhibitors and should be considered. However, there are no clinical data with this dose adjustment in patients receiving strong CYP3A4 inhibitors. If the strong inhibitor is discontinued, a washout period of approximately 1 week should be allowed before the TYKERB dose is adjusted upward to the indicated dose [see Drug Interactions (7.2)].

Concomitant Strong CYP3A4 Inducers: The concomitant use of strong CYP3A4 inducers should be avoided (e.g., dexamethasone, phenytoin, carbamazepine, rifampin, rifabutin, rifapentine, phenobarbital, St. John’s wort). If patients must be coadministered a strong CYP3A4 inducer, based on pharmacokinetic studies, the dose of TYKERB should be titrated gradually from 1,250 mg/day up to 4,500 mg/day (HER2-positive metastatic breast cancer indication) or from 1,500 mg/day up to 5,500 mg/day (hormone receptor-positive, HER2-positive breast cancer indication) based on tolerability. This dose of TYKERB is predicted to adjust the lapatinib AUC to the range observed without inducers and should be considered. However, there are no clinical data with this dose adjustment in patients receiving strong CYP3A4 inducers. If the strong inducer is discontinued, the TYKERB dose should be reduced to the indicated dose [see Drug Interactions (7.2)].

Other Toxicities: Discontinuation or interruption of dosing with TYKERB may be considered when patients develop greater than or equal to Grade 2 NCI CTCAE toxicity, and can be restarted at the standard dose of 1,250 or 1,500 mg/day when the toxicity improves to Grade 1 or less. If the toxicity recurs, then TYKERB in combination with capecitabine should be restarted at a lower dose (1,000 mg/day) and in combination with letrozole should be restarted at a lower dose of 1,250 mg/day.

See manufacturer’s prescribing information for the coadministered product dosage adjustment guidelines in the event of toxicity and other relevant safety information or contraindications.

3 DOSAGE FORMS AND STRENGTHS

250 mg tablets — oval, biconvex, orange, film-coated with ‘GS XJG’ debossed on one side.

4 CONTRAINDICATIONS

TYKERB is contraindicated in patients with known severe hypersensitivity (e.g., anaphylaxis) to this product or any of its components.

5 WARNINGS AND PRECAUTIONS

5.1 Decreased Left Ventricular Ejection Fraction

TYKERB has been reported to decrease LVEF [see Adverse Reactions (6.1)]. In clinical trials, the majority (greater than 57%) of LVEF decreases occurred within the first 12 weeks of treatment; however, data on long-term exposure are limited. Caution should be taken if TYKERB is to be administered to patients with conditions that could impair left ventricular function. LVEF should be evaluated in all patients prior to initiation of treatment with TYKERB to ensure that the patient has a baseline LVEF that is within the institution’s normal limits. LVEF should continue to be evaluated during treatment with TYKERB to ensure that LVEF does not decline below the institution’s normal limits [see Dosage and Administration (2.2)].

5.2 Hepatotoxicity

Hepatotoxicity [alanine aminotransferase (ALT) or aspartate aminotransferase (AST) greater than 3 times the upper limit of normal (ULN) and total bilirubin greater than 2 times the ULN] has been observed in clinical trials (less than 1% of patients) and postmarketing experience. The hepatotoxicity may be severe and deaths have been reported. Causality of the deaths is uncertain. The hepatotoxicity may occur days to several months after initiation of treatment. Liver function tests (transaminases, bilirubin, and alkaline phosphatase) should be monitored before initiation of treatment, every 4 to 6 weeks during treatment, and as clinically indicated. If changes in liver function are severe, therapy with TYKERB should be discontinued and patients should not be retreated with TYKERB [see Adverse Reactions (6.1)].

5.3 Patients With Severe Hepatic Impairment

If TYKERB is to be administered to patients with severe preexisting hepatic impairment, dose reduction should be considered [see Dosage and Administration (2.2) and Use in Specific Populations (8.7)]. In patients who develop severe hepatotoxicity while on therapy, TYKERB should be discontinued and patients should not be retreated with TYKERB [see Warnings and Precautions (5.2)].

5.4 Diarrhea

Diarrhea has been reported during treatment with TYKERB [see Adverse Reactions (6.1)]. The diarrhea may be severe, and deaths have been reported. Diarrhea generally occurs early during treatment with TYKERB, with almost half of those patients with diarrhea first experiencing it within 6 days. This usually lasts 4 to 5 days. TYKERB-induced diarrhea is usually low-grade, with severe diarrhea of NCI CTCAE Grades 3 and 4 occurring in less than 10% and less than 1% of patients, respectively. Early identification and intervention is critical for the optimal management of diarrhea. Patients should be instructed to report any change in bowel patterns immediately. Prompt treatment of diarrhea with antidiarrheal agents (such as loperamide) after the first unformed stool is recommended. Severe cases of diarrhea may require administration of oral or intravenous electrolytes and fluids, use of antibiotics, such as fluoroquinolones (especially if diarrhea is persistent beyond 24 hours, there is fever, or Grade 3 or 4 neutropenia), and interruption or discontinuation of therapy with TYKERB [see Dosage and Administration (2.2)].

5.5 Interstitial Lung Disease/Pneumonitis

TYKERB has been associated with interstitial lung disease (ILD) and pneumonitis in monotherapy or in combination with other chemotherapies [see Adverse Reactions (6.1)]. Patients should be monitored for pulmonary symptoms indicative of ILD or pneumonitis. TYKERB should be discontinued in patients who experience pulmonary symptoms indicative of ILD/pneumonitis, which are greater than or equal to Grade 3 (NCI CTCAE v3.0).

5.6 QT Prolongation

A concentration-dependent QT prolongation has been associated with TYKERB [see Clinical Pharmacology (12.2)]. Monitor patients who have or may develop prolongation of QTc during treatment with TYKERB. These conditions include patients with hypokalemia or hypomagnesemia, with congenital long QT syndrome, patients taking antiarrhythmic medicines or other medicinal products with known risk for QT prolongation/ Torsades de Pointes, and cumulative high-dose anthracycline therapy. Correct hypokalemia or hypomagnesemia prior to TYKERB administration.

5.7 Severe Cutaneous Reactions

Severe cutaneous reactions have been reported with TYKERB. If life-threatening reactions, such as erythema multiforme, Stevens-Johnson syndrome, or toxic epidermal necrolysis (e.g., progressive skin rash often with blisters or mucosal lesions) are suspected, discontinue treatment with TYKERB.

5.8 Embryo-Fetal Toxicity

Based on its mechanism of action and findings in animal studies, TYKERB can cause fetal harm when administered to a pregnant woman. In animal reproductive studies, administration of lapatinib to pregnant rats during the period of organogenesis and through lactation led to death of offspring within the first 4 days after birth at maternal exposures that were ≥ 3.3 times the human clinical exposure based on AUC following 1,250 mg dose of lapatinib plus capecitabine. When administered to pregnant animals during the period of organogenesis, lapatinib caused fetal anomalies (rats) or abortions (rabbits) at maternally toxic doses (with maternal exposures approximately 6.4 and 0.2 times, respectively, the human clinical exposure based on AUC following 1,250 mg dose of lapatinib plus capecitabine).

Advise pregnant women and females of reproductive potential of the potential risk to the fetus [see Use in Specific Populations (8.1) and Clinical Pharmacology (12.1)]. Verify the pregnancy status of females of reproductive potential prior to initiation of TYKERB. Advise females of reproductive potential to use effective contraception during treatment with TYKERB and for 1 week after the last dose. Advise male patients with female partners of reproductive potential to use effective contraception during treatment with TYKERB and for 1 week after the last dose [see Use in Specific Populations (8.1, 8.3)].

6 ADVERSE REACTIONS

6.1 Clinical Trials Experience

Because clinical trials are conducted under widely varying conditions, adverse reaction rates observed in the clinical trials of a drug cannot be directly compared to rates in the clinical trials of another drug and may not reflect the rates observed in practice.

HER2-Positive Metastatic Breast Cancer: The safety of TYKERB has been evaluated in more than 12,000 patients in clinical trials. The efficacy and safety of TYKERB in combination with capecitabine in breast cancer was evaluated in 198 patients in a randomized, Phase 3 trial [see Clinical Studies (14.1)]. Adverse reactions, which occurred in at least 10% of patients in either treatment arm and were higher in the combination arm, are shown in Table 1.

The most common adverse reactions (greater than 20%) during therapy with TYKERB plus capecitabine were gastrointestinal (diarrhea, nausea, and vomiting), dermatologic (palmar-plantar erythrodysesthesia and rash), and fatigue. Diarrhea was the most common adverse reaction resulting in discontinuation of study medication.

The most common Grades 3 and 4 adverse reactions (NCI CTCAE v3.0) were diarrhea and palmar-plantar erythrodysesthesia. Selected laboratory abnormalities are shown in Table 2.

Table 1. Adverse Reactions Occurring in Greater Than or Equal to 10% of Patients
 | TYKERB 1,250 mg/day + Capecitabine 2,000 mg/m^2/day |  |  | Capecitabine 2,500 mg/m^2/day
 | (N = 198) |  |  | (N = 191)
 | All Gradesa | Grade 3 | Grade 4 | All Gradesa | Grade 3 | Grade 4
Reactions | % | % | % | % | % | %
Gastrointestinal disorders
Diarrhea | 65 | 13 | 1 | 40 | 10 | 0
Nausea | 44 | 2 | 0 | 43 | 2 | 0
Vomiting | 26 | 2 | 0 | 21 | 2 | 0
Stomatitis | 14 | 0 | 0 | 11 | < 1 | 0
Dyspepsia | 11 | < 1 | 0 | 3 | 0 | 0
Skin and subcutaneous tissue disorders
Palmar-plantar erythrodysesthesia | 53 | 12 | 0 | 51 | 14 | 0
Rashb | 28 | 2 | 0 | 14 | 1 | 0
Dry skin | 10 | 0 | 0 | 6 | 0 | 0
General disorders and administration site conditions
Mucosal inflammation | 15 | 0 | 0 | 12 | 2 | 0
Musculoskeletal and connective tissue disorders
Pain in extremity | 12 | 1 | 0 | 7 | < 1 | 0
Back pain | 11 | 1 | 0 | 6 | < 1 | 0
Respiratory, thoracic, and mediastinal disorders
Dyspnea | 12 | 3 | 0 | 8 | 2 | 0
Psychiatric disorders
Insomnia | 10 | < 1 | 0 | 6 | 0 | 0
a NCI CTCAE v3.0.
b Grade 3 dermatitis acneiform was reported in less than 1% of patients in the group receiving TYKERB plus capecitabine.

Table 2. Selected Laboratory Abnormalities
 | TYKERB 1,250 mg/day + Capecitabine 2,000 mg/m^2/day |  |  | Capecitabine 2,500 mg/m^2/day
 | All Gradesa | Grade 3 | Grade 4 | All Gradesa | Grade 3 | Grade 4
Parameters | % | % | % | % | % | %
Hematologic
Hemoglobin | 56 | < 1 | 0 | 53 | 1 | 0
Platelets | 18 | < 1 | 0 | 17 | < 1 | < 1
Neutrophils | 22 | 3 | < 1 | 31 | 2 | 1
Hepatic
Total Bilirubin | 45 | 4 | 0 | 30 | 3 | 0
AST | 49 | 2 | < 1 | 43 | 2 | 0
ALT | 37 | 2 | 0 | 33 | 1 | 0
Abbreviations: ALT, alanine aminotransferase; AST, aspartate aminotransferase.
a NCI CTCAE v3.0.

Hormone Receptor-Positive, Metastatic Breast Cancer: In a randomized, Phase 3 clinical trial of patients (N = 1286) with hormone receptor-positive, metastatic breast cancer, who had not received chemotherapy for their metastatic disease, patients received letrozole with or without TYKERB. In this trial, the safety profile of TYKERB was consistent with previously reported results from trials of TYKERB in the advanced or metastatic breast cancer population. Adverse reactions, which occurred in at least 10% of patients in either treatment arm and were higher in the combination arm are shown in Table 3. Selected laboratory abnormalities are shown in Table 4.

Table 3. Adverse Reactions Occurring in Greater Than or Equal to 10% of Patients
 | TYKERB 1,500 mg/day + Letrozole 2.5 mg/day |  |  | Letrozole 2.5 mg/day
 | (N = 654) |  |  | (N = 624)
 | All Gradesa | Grade 3 | Grade 4 | All Gradesa | Grade 3 | Grade 4
Reactions | % | % | % | % | % | %
Gastrointestinal disorders
Diarrhea | 64 | 9 | < 1 | 20 | < 1 | 0
Nausea | 31 | < 1 | 0 | 21 | < 1 | 0
Vomiting | 17 | 1 | < 1 | 11 | < 1 | < 1
Anorexia | 11 | < 1 | 0 | 9 | < 1 | 0
Skin and subcutaneous tissue disorders
Rashb | 44 | 1 | 0 | 13 | 0 | 0
Dry skin | 13 | < 1 | 0 | 4 | 0 | 0
Alopecia | 13 | < 1 | 0 | 7 | 0 | 0
Pruritus | 12 | < 1 | 0 | 9 | < 1 | 0
Nail disorder | 11 | < 1 | 0 | < 1 | 0 | 0
General disorders and administration site conditions
Fatigue | 20 | 2 | 0 | 17 | < 1 | 0
Asthenia | 12 | < 1 | 0 | 11 | < 1 | 0
Nervous system disorders
Headache | 14 | < 1 | 0 | 13 | < 1 | 0
Respiratory, thoracic, and mediastinal disorders
Epistaxis | 11 | < 1 | 0 | 2 | < 1 | 0
a NCI CTCAE v3.0.
b In addition to the rash reported under "Skin and subcutaneous tissue disorders", 3 additional subjects in each treatment arm had rash under "Infections and infestations"; none were Grade 3 or 4.

Table 4. Selected Laboratory Abnormalities
 | TYKERB 1,500 mg/day + Letrozole 2.5 mg/day |  |  | Letrozole 2.5 mg/day
 | All Gradesa | Grade 3 | Grade 4 | All Gradesa | Grade 3 | Grade 4
Hepatic Parameters | % | % | % | % | % | %
AST | 53 | 6 | 0 | 36 | 2 | < 1
ALT | 46 | 5 | < 1 | 35 | 1 | 0
Total Bilirubin | 22 | < 1 | < 1 | 11 | 1 | < 1
Abbreviations: ALT, alanine aminotransferase; AST, aspartate aminotransferase.
a NCI CTCAE v3.0.

Hormone Receptor-Positive, HER2+ Metastatic Breast Cancer: In another randomized, Phase 3 clinical trial of postmenopausal patients (N = 355) with hormone receptor positive (HR+), HER2-positive metastatic breast cancer (MBC) which had progressed after prior trastuzumab-containing chemotherapy and endocrine therapies, patients received TYKERB with trastuzumab and an aromatase inhibitor (AI) (letrozole, exemestane, or anastrozole), TYKERB with an AI, or trastuzumab with an AI. In this trial, the safety profile of the treatment groups was consistent with the known safety of these agents. The most frequent study treatment-related AEs (> 10%) in each of the TYKERB-containing treatment arms were diarrhea, rash, paronychia, nausea, stomatitis, dermatitis acneiform, and decreased appetite, which were infrequent to absent in the trastuzumab treatment arm. The frequency of cardiac AEs (mostly decrease in ejection fraction) was 7% in the TYKERB+trastuzumab+AI group, 2% in the TYKERB+AI group and 3% in the trastuzumab+AI group. Adverse reactions which occurred in at least 10% of patients in the treatment arms are shown in Table 5.

Table 5. Adverse Reactions Occurring in Greater Than or Equal to 10% of Patients
 | TYKERB (1,000 mg) + Trastuzumab + AI |  |  | TYKERB (1,500 mg) + AI |  |  | Trastuzumab + AI
 | (N = 118) |  |  | (N = 119) |  |  | (N = 116)
 | All Gradesa | Grade 3 | Grade 4 | All Gradesa | Grade 3 | Grade 4 | All Gradesa | Grade 3 | Grade 4
Reactions | (%) | (%) | (%) | (%) | (%) | (%) | (%) | (%) | (%)
Gastrointestinal disorders
Diarrhea | 69 | 13 | 0 | 51 | 6 | 0 | 9 | 0 | 0
Nausea | 22 | 0 | 0 | 22 | 2 | 0 | 9 | 0 | 0
Stomatitis | 17 | 0 | 0 | 13 | < 1 | 0 | 3 | 0 | 0
Vomiting | 10 | 0 | 0 | 14 | 0 | 0 | < 1 | < 1 | 0
Skin and subcutaneous tissue disorders
Rashb | 54 | 0 | 0 | 44 | 3 | 0 | 5 | 0 | 0
Palmar-plantar erythrodysesthesia | 10 | 0 | 0 | 8 | < 1 | 0 | < 1 | 0 | 0
Alopecia | 10 | 0 | 0 | 7 | 0 | 0 | 2 | 0 | 0
General disorders and administration site conditions
Fatigue | 12 | < 1 | 0 | 14 | 2 | 0 | 10 | 0 | 0
Musculoskeletal and connective tissue disorders
Arthralgia | 13 | < 1 | 0 | 14 | 0 | 0 | 12 | 0 | 0
Pain in extremity | 7 | < 1 | 0 | 10 | 0 | 0 | 3 | 0 | 0
Respiratory, thoracic, and mediastinal disorders
Cough | 8 | 0 | 0 | 8 | 0 | 0 | 15 | 0 | 0
Metabolism and nutrition disorders
Decreased appetite | 18 | 0 | 0 | 13 | 0 | 0 | 3 | 0 | 0
Infections and infestations
Paronychia | 30 | 0 | 0 | 15 | 2 | 0 | 0 | 0 | 0
Investigations
Alanine aminotransferase increased | 7 | 0 | 0 | 15 | 3 | < 1 | 6 | 4 | 0
Aspartate aminotransferase increased | 6 | 0 | 0 | 17 | 5 | 0 | 9 | 4 | 0
Nervous system disorders
Headache | 5 | 0 | 0 | 16 | 2 | 0 | 10 | < 1 | 0
a NCI CTCAE v3.0.
b Includes multiple adverse reaction terms for rash.

Decreases in Left Ventricular Ejection Fraction: Due to potential cardiac toxicity with HER2 (ErbB2) inhibitors, LVEF was monitored in clinical trials at approximately 8-week intervals. LVEF decreases were defined as signs or symptoms of deterioration in left ventricular cardiac function that are greater than or equal to Grade 3 (NCI CTCAE v3.0), or a greater than or equal to 20% decrease in left ventricular cardiac ejection fraction relative to baseline which is below the institution's lower limit of normal. Among 198 patients who received combination treatment with TYKERB/capecitabine, 3 experienced Grade 2 and one had Grade 3 LVEF adverse reactions (NCI CTCAE v3.0). Among 654 patients who received combination treatment with TYKERB/letrozole, 26 patients experienced Grade 1 or 2 and 6 patients had Grade 3 or 4 LVEF adverse reactions [see Warnings and Precautions (5.1)].

Hepatotoxicity: TYKERB has been associated with hepatotoxicity [see Boxed Warning and Warnings and Precautions (5.2)].

Interstitial Lung Disease/Pneumonitis: TYKERB has been associated with ILD and pneumonitis in monotherapy or in combination with other chemotherapies [see Warnings and Precautions (5.5)].

6.2 Postmarketing Experience

The following adverse reactions have been identified during post-approval use of TYKERB. Because these reactions are reported voluntarily from a population of uncertain size, it is not always possible to reliably estimate their frequency or establish a causal relationship to drug exposure.

Immune System Disorders: Hypersensitivity reactions, including anaphylaxis [see Contraindications (4)].

Skin and Subcutaneous Tissue Disorders: Nail disorders, including paronychia. Severe cutaneous adverse reactions, including Stevens-Johnson syndrome, toxic epidermal necrolysis (TEN), skin fissures.

Cardiac Disorders: Ventricular arrhythmias/Torsades de Pointes. Electrocardiogram (ECG) QT prolongation.

7 DRUG INTERACTIONS

7.1 Effects of Lapatinib on Drug-Metabolizing Enzymes and Drug Transport Systems

Lapatinib inhibits CYP3A4, CYP2C8, and P-glycoprotein (P-gp, ABCB1) in vitro at clinically relevant concentrations and is a weak inhibitor of CYP3A4 in vivo. Caution should be exercised and dose reduction of the concomitant substrate drug should be considered when dosing TYKERB concurrently with medications with narrow therapeutic windows that are substrates of CYP3A4, CYP2C8, or P-gp. Lapatinib did not significantly inhibit the following enzymes in human liver microsomes: CYP1A2, CYP2C9, CYP2C19, and CYP2D6 or UGT enzymes in vitro, however, the clinical significance is unknown.

Midazolam: Following coadministration of TYKERB and midazolam (CYP3A4 substrate), 24-hour systemic exposure (AUC) of orally administered midazolam increased 45%, while 24-hour AUC of intravenously administered midazolam increased 22%.

Paclitaxel: In cancer patients receiving TYKERB and paclitaxel (CYP2C8 and P-gp substrate), 24-hour systemic exposure (AUC) of paclitaxel was increased 23%. This increase in paclitaxel exposure may have been underestimated from the in vivo evaluation due to study design limitations.

Digoxin: Following coadministration of TYKERB and digoxin (P-gp substrate), systemic AUC of an oral digoxin dose increased approximately 2.8-fold. Serum digoxin concentrations should be monitored prior to initiation of TYKERB and throughout coadministration. If digoxin serum concentration is greater than 1.2 ng/mL, the digoxin dose should be reduced by half.

7.2 Drugs That Inhibit or Induce Cytochrome P450 3A4 Enzymes

Lapatinib undergoes extensive metabolism by CYP3A4, and concomitant administration of strong inhibitors or inducers of CYP3A4 alter lapatinib concentrations significantly (see Ketoconazole and Carbamazepine sections, below). Dose adjustment of TYKERB should be considered for patients who must receive concomitant strong inhibitors or concomitant strong inducers of CYP3A4 enzymes [see Dosage and Administration (2.2)].

Ketoconazole: In healthy subjects receiving ketoconazole, a CYP3A4 inhibitor, at 200 mg twice daily for 7 days, systemic exposure (AUC) to lapatinib was increased to approximately 3.6-fold of control and half-life increased to 1.7-fold of control.

Carbamazepine: In healthy subjects receiving the CYP3A4 inducer, carbamazepine, at 100 mg twice daily for 3 days and 200 mg twice daily for 17 days, systemic exposure (AUC) to lapatinib was decreased approximately 72%.

7.3 Drugs That Inhibit Drug Transport Systems

Lapatinib is a substrate of the efflux transporter P-glycoprotein (P-gp, ABCB1). If TYKERB is administered with drugs that inhibit P-gp, increased concentrations of lapatinib are likely, and caution should be exercised.

7.4 Acid-Reducing Agents

The aqueous solubility of lapatinib is pH dependent, with higher pH resulting in lower solubility. However, esomeprazole, a proton pump inhibitor, administered at a dose of 40 mg once daily for 7 days, did not result in a clinically meaningful reduction in lapatinib steady-state exposure.

8 USE IN SPECIFIC POPULATIONS

8.1 Pregnancy

Risk Summary

Based on findings in animal studies and its mechanism of action, TYKERB can cause fetal harm when administered to a pregnant woman [see Clinical Pharmacology (12.1)]. There are no available human data to inform of the drug-associated risks. In an animal reproduction study, administration of lapatinib to pregnant rats during organogenesis and through lactation led to death of offspring within the first 4 days after birth at maternal exposures that were ≥ 3.3 times the human clinical exposure based on AUC following 1,250 mg dose of lapatinib plus capecitabine. When administered to pregnant animals during the period of organogenesis, lapatinib caused fetal anomalies (rats) or abortions (rabbits) at maternally toxic doses (see Data).

Advise pregnant women and females of reproductive potential of the potential risk to the fetus.

The background risk of major birth defects and miscarriage for the indicated population is unknown; however, in the U.S. general population, the estimated background risk of major birth defects is 2% to 4% and of miscarriage is 15% to 20% of clinically recognized pregnancies.

Data

Animal Data

In embryo-fetal development studies in rats and rabbits, pregnant animals received oral doses of lapatinib at 30, 60, and 120 mg/kg/day during the period of organogenesis. Minor anomalies (left-sided umbilical artery, cervical rib, and precocious ossification) occurred in rats at the maternally toxic dose of 120 mg/kg/day (approximately 6.4 times the human clinical exposure based on AUC following 1,250 mg dose of lapatinib plus capecitabine). In rabbits, lapatinib was associated with maternal toxicity at 60 and 120 mg/kg/day (approximately 0.07 and 0.2 times the human clinical exposure, respectively, based on AUC following 1,250 mg dose of lapatinib plus capecitabine) and abortions at 120 mg/kg/day. Maternal toxicity was associated with decreased fetal body weights and minor skeletal variations.

In a pre- and post-natal development study, rats were given oral doses of 20, 60, and 120 mg/kg/day during gestation through lactation up to weaning. In rats, doses of 60 and 120 mg/kg/day (approximately 3.3 and 6.4 times the human clinical exposure, respectively, based on AUC following 1,250 mg dose of lapatinib plus capecitabine) led to decrease in F1 postnatal survival (91% and 34% of the pups died by the fourth day after birth, at 60 and 120 mg/kg/day, respectively).

8.2 Lactation

Risk Summary

There are no data on the presence of lapatinib in human milk, or its effects on the breastfed child, or milk production. Because of the potential for serious adverse reactions in a breastfed child from TYKERB, advise lactating women not to breastfeed during treatment with TYKERB and for 1 week after the last dose.

8.3 Females and Males of Reproductive Potential

Pregnancy Testing

Verify the pregnancy status of females of reproductive potential prior to the initiation of TYKERB.

Contraception

Females

Based on findings in animal studies, TYKERB can cause fetal harm when administered to a pregnant woman [see Use in Specific Populations (8.1)]. Advise females of reproductive potential to use effective contraception during treatment with TYKERB and for 1 week after the last dose.

Males

Based on findings in animal reproduction studies, advise male patients with female partners of reproductive potential to use effective contraception during treatment with TYKERB and for 1 week after the last dose [see Use in Specific Populations (8.1)].

8.4 Pediatric Use

The safety and effectiveness of TYKERB in pediatric patients have not been established.

8.5 Geriatric Use

Of the total number of metastatic breast cancer patients in clinical studies of TYKERB in combination with capecitabine (N = 198), 17% were 65 years of age and older, and 1% were 75 years of age and older. Of the total number of hormone receptor-positive, HER2-positive metastatic breast cancer patients in clinical studies of TYKERB in combination with letrozole (N = 642), 44% were 65 years of age and older, and 12% were 75 years of age and older. No overall differences in safety or effectiveness were observed between elderly subjects and younger subjects, and other reported clinical experience has not identified differences in responses between the elderly and younger patients, but greater sensitivity of some older individuals cannot be ruled out.

8.6 Renal Impairment

Lapatinib pharmacokinetics have not been specifically studied in patients with renal impairment or in patients undergoing hemodialysis. There is no experience with TYKERB in patients with severe renal impairment. However, renal impairment is unlikely to affect the pharmacokinetics of lapatinib given that less than 2% (lapatinib and metabolites) of an administered dose is eliminated by the kidneys.

8.7 Hepatic Impairment

The pharmacokinetics of lapatinib were examined in subjects with preexisting moderate (n = 8) or severe (n = 4) hepatic impairment (Child-Pugh Class B/C, respectively) and in 8 healthy control subjects. Systemic exposure (AUC) to lapatinib after a single oral 100 mg dose increased approximately 14% and 63% in subjects with moderate and severe preexisting hepatic impairment, respectively. Administration of TYKERB in patients with severe hepatic impairment should be undertaken with caution due to increased exposure to the drug. A dose reduction should be considered for patients with severe preexisting hepatic impairment [see Dosage and Administration (2.2)]. In patients who develop severe hepatotoxicity while on therapy, TYKERB should be discontinued and patients should not be retreated with TYKERB [see Warnings and Precautions (5.2)].

10 OVERDOSAGE

There is no known antidote for overdoses of TYKERB. The maximum oral doses of lapatinib that have been administered in clinical trials are 1,800 mg once daily. More frequent ingestion of TYKERB could result in serum concentrations exceeding those observed in clinical trials and could result in increased toxicity. Therefore, missed doses should not be replaced and dosing should resume with the next scheduled daily dose.

Asymptomatic and symptomatic cases of overdose have been reported. The doses ranged from 2,500 to 9,000 mg daily and where reported, the duration varied between 1 and 17 days. Symptoms observed include TYKERB-associated events [see Adverse Reactions (6.1)] and in some cases sore scalp, sinus tachycardia (with otherwise normal ECG), and/or mucosal inflammation.

Because TYKERB is not significantly renally excreted and is highly bound to plasma proteins, hemodialysis would not be expected to be an effective method to enhance the elimination of lapatinib.

Treatment of overdose with TYKERB should consist of general supportive measures.

11 DESCRIPTION

Lapatinib is a small molecule and a member of the 4-anilinoquinazoline class of kinase inhibitors. It is present as the monohydrate of the ditosylate salt, with chemical name N-(3-chloro-4-{[(3-fluorophenyl)methyl]oxy}phenyl)-6-[5-({[2-(methylsulfonyl)ethyl]amino}methyl)-2-furanyl]-4-quinazolinamine bis(4-methylbenzenesulfonate) monohydrate. It has the molecular formula C29H26ClFN4O4S (C7H8O3S)2 H2O and a molecular weight of 943.5 g/mol. Lapatinib ditosylate monohydrate has the following chemical structure:

Lapatinib is a yellow solid, and its solubility in water is 0.007 mg/mL and in 0.1N HCl is 0.001 mg/mL at 25°C.

Each 250 mg tablet of TYKERB contains 405 mg of lapatinib ditosylate monohydrate, equivalent to 398 mg of lapatinib ditosylate or 250 mg lapatinib free base.

The inactive ingredients of TYKERB are: Tablet Core: Magnesium stearate, microcrystalline cellulose, povidone, sodium starch glycolate. Coating: Orange film-coat: FD&C yellow No. 6/sunset yellow FCF aluminum lake, hypromellose, macrogol/PEG 400, polysorbate 80, titanium dioxide.

12 CLINICAL PHARMACOLOGY

12.1 Mechanism of Action

Lapatinib is a 4-anilinoquinazoline kinase inhibitor of the intracellular tyrosine kinase domains of both Epidermal Growth Factor Receptor (EGFR [ErbB1]) and of Human Epidermal Receptor Type 2 (HER2 [ErbB2]) receptors (estimated Kiapp values of 3nM and 13nM, respectively) with a dissociation half-life of greater than or equal to 300 minutes. Lapatinib inhibits ErbB-driven tumor cell growth in vitro and in various animal models.

An additive effect was demonstrated in an in vitro study when lapatinib and 5-FU (the active metabolite of capecitabine) were used in combination in the 4-tumor cell lines tested. The growth inhibitory effects of lapatinib were evaluated in trastuzumab-conditioned cell lines. Lapatinib retained significant activity against breast cancer cell lines selected for long-term growth in trastuzumab-containing medium in vitro. These in vitro findings suggest non-cross-resistance between these two agents.

Hormone receptor-positive breast cancer cells (with ER [Estrogen Receptor] and/or PgR [Progesterone Receptor]) that coexpress the HER2 tend to be resistant to established endocrine therapies. Similarly, hormone receptor-positive breast cancer cells that initially lack EGFR or HER2 upregulate these receptor proteins as the tumor becomes resistant to endocrine therapy.

12.2 Pharmacodynamics

Cardiac Electrophysiology

The effect of lapatinib on the QT-interval was evaluated in a single-blind, placebo-controlled, single sequence (placebo and active treatment) crossover study in patients with advanced solid tumors (N = 58). During the 4-day treatment period, three doses of matching placebo were administered 12 hours apart in the morning and evening on Day 1 and in the morning on Day 2. This was followed by three doses of lapatinib 2,000 mg (1.3 – 1.6 times the recommended dosage) administered in the same way. Measurements, including ECGs and pharmacokinetic samples were done at baseline and at the same time points on Day 2 and Day 4. In the evaluable population of subjects who had complete dosing and ECG assessments (N = 37), the maximum mean ΔΔQTcF (90% CI) of 8.75 ms (4.08, 13.42) was observed 10 hours after ingestion of the third dose of lapatinib 2000 mg. The ΔΔQTcF exceeded the 5 ms threshold and the upper bound 90% CIs exceeded the 10 ms threshold at multiple time points.

There was a concentration-dependent increase in QTcF effects [see Warnings and Precautions (5.6)].

12.3 Pharmacokinetics

Absorption: Absorption following oral administration of TYKERB is incomplete and variable. Serum concentrations appear after a median lag time of 0.25 hours (range 0 to 1.5 hours). Peak plasma concentrations (Cmax) of lapatinib are achieved approximately 4 hours after administration. Daily dosing of TYKERB results in achievement of steady state within 6 to 7 days, indicating an effective half-life of 24 hours.

At the dose of 1,250 mg daily, steady-state geometric mean [95% confidence interval (CI)] values of Cmax were 2.43 mcg/mL (1.57 to 3.77 mcg/mL) and AUC were 36.2 mcg.h/mL (23.4 to 56 mcg.h/mL).

Divided daily doses of TYKERB resulted in approximately 2-fold higher exposure at steady state (steady-state AUC) compared to the same total dose administered once daily.

Systemic exposure to lapatinib is increased when administered with food. Lapatinib AUC values were approximately 3- and 4-fold higher (Cmax approximately 2.5- and 3-fold higher) when administered with a low-fat (5% fat-500 calories) or with a high-fat (50% fat-1000 calories) meal, respectively.

Distribution: Lapatinib is highly bound (greater than 99%) to albumin and alpha-1 acid glycoprotein. In vitro studies indicate that lapatinib is a substrate for the transporters breast cancer-resistance protein (BCRP, ABCG2) and P-glycoprotein (P-gp, ABCB1). Lapatinib has also been shown to inhibit P-gp, BCRP, and the hepatic uptake transporter OATP 1B1, in vitro at clinically relevant concentrations.

Metabolism: Lapatinib undergoes extensive metabolism, primarily by CYP3A4 and CYP3A5, with minor contributions from CYP2C19 and CYP2C8 to a variety of oxidated metabolites, none of which accounts for more than 14% of the dose recovered in the feces or 10% of lapatinib concentration in plasma.

Elimination: At clinical doses, the terminal phase half-life following a single dose was 14.2 hours; accumulation with repeated dosing indicates an effective half-life of 24 hours.

Elimination of lapatinib is predominantly through metabolism by CYP3A4/5 with negligible (less than 2%) renal excretion. Recovery of parent lapatinib in feces accounts for a median of 27% (range 3% to 67%) of an oral dose.

Effects of Age, Gender, or Race: Studies of the effects of age, gender, or race on the pharmacokinetics of lapatinib have not been performed.

12.5 Pharmacogenomics

The HLA alleles DQA1*02:01 and DRB1*07:01 were associated with hepatotoxicity reactions in a genetic substudy of a monotherapy trial with TYKERB (n = 1194). Severe liver injury (ALT greater than 5 times the upper limit of normal, NCI CTCAE Grade 3) occurred in 2% of patients overall; the incidence of severe liver injury among DQA1*02:01 or DRBI*07:01 allele carriers was 8% versus 0.5% in non-carriers. These HLA alleles are present in approximately 15% to 25% of Caucasian, Asian, African, and Hispanic populations and 1% in Japanese populations. Liver function should be monitored in all patients receiving therapy with TYKERB regardless of genotype.

13 NONCLINICAL TOXICOLOGY

13.1 Carcinogenesis, Mutagenesis, Impairment of Fertility

In carcinogenicity studies, lapatinib was administered orally for up to 104 weeks at doses of 75 and 150 mg/kg/day in male mice and 75, 150, and 300 mg/kg/day in female mice (approximately 0.7 to 2 times the expected human clinical exposure based on AUC for a clinical dose of 1,250 mg/day plus capecitabine) and 60, 120, 240, and 500 mg/kg/day (approximately 0.6 to 2.3 times the expected human clinical exposure based on AUC) in male rats, and 20, 60, and 180 mg/kg/day (approximately 1.4 to 10 times the expected human clinical exposure based on AUC for a clinical dose of 1,250 mg/day plus capecitabine) in female rats. There was no evidence of carcinogenicity in mice. In male rats, there was an increased incidence of whole body combined hemangiomas and hemangiosarcomas.

Lapatinib was not clastogenic or mutagenic in the Chinese hamster ovary chromosome aberration assay, microbial mutagenesis (Ames) assay, human peripheral lymphocyte chromosome aberration assay or the in vivo rat bone marrow chromosome aberration assay at single doses up to 2,000 mg/kg.

There were no effects on male or female rat mating or fertility at doses up to 120 mg/kg/day in females and 180 mg/kg/day in males (approximately 6.4 times and 2.6 times the expected human clinical exposure based on AUC following 1,250 mg dose of lapatinib plus capecitabine, respectively). The effect of lapatinib on human fertility is unknown. However, when female rats were given oral doses of lapatinib during breeding and through the first 6 days of gestation, a significant decrease in the number of live fetuses was seen at 120 mg/kg/day and in the fetal body weights at greater than or equal to 60 mg/kg/day (approximately 6.4 times and 3.3 times the expected human clinical exposure based on AUC following 1,250 mg dose of lapatinib plus capecitabine, respectively).

13.2 Animal Toxicology and/or Pharmacology

In 104-week repeat-dose studies in rodents, severe skin lesions that led to lethality were seen at the highest doses tested (300 mg/kg/day) in male mice and female rats. There was also an increase in renal infarcts and papillary necrosis in female rats at greater than or equal to 60 mg/kg/day and greater than or equal to 180 mg/kg/day, respectively (approximately 7 and 10 times the expected human clinical exposure based on AUC, respectively). The relevance of these findings for humans is uncertain.

14 CLINICAL STUDIES

14.1 HER2-Positive Metastatic Breast Cancer

The efficacy and safety of TYKERB in combination with capecitabine in breast cancer were evaluated in a randomized, Phase 3 trial. Patients eligible for enrollment had HER2 (ErbB2) overexpressing (IHC 3+ or IHC 2+ confirmed by FISH), locally advanced or metastatic breast cancer, progressing after prior treatment that included anthracyclines, taxanes, and trastuzumab.

Patients were randomized to receive either TYKERB 1,250 mg once daily (continuously) plus capecitabine 2,000 mg/m^2/day on Days 1-14 every 21 days, or to receive capecitabine alone at a dose of 2,500 mg/m^2/day on Days 1-14 every 21 days. The endpoint was time to progression (TTP). TTP was defined as time from randomization to tumor progression or death related to breast cancer. Based on the results of a pre-specified interim analysis, further enrollment was discontinued. Three hundred and ninety-nine (399) patients were enrolled in this study. The median age was 53 years and 14% were older than 65 years. Ninety-one percent (91%) were Caucasian. Ninety-seven percent (97%) had stage IV breast cancer, 48% were estrogen receptor+ (ER+) or progesterone receptor+ (PR+), and 95% were ErbB2 IHC 3+ or IHC 2+ with FISH confirmation. Approximately 95% of patients had prior treatment with anthracyclines, taxanes, and trastuzumab.

Efficacy analyses 4 months after the interim analysis are presented in Table 6, Figure 1, and Figure 2.

Table 6. Efficacy Results
 | Independent Assessmenta |  | Investigator Assessment
 | TYKERB 1,250 mg/day + Capecitabine 2,000 mg/m^2/day | Capecitabine 2,500 mg/m^2/day | TYKERB 1,250 mg/day + Capecitabine 2,000 mg/m^2/day | Capecitabine 2,500 mg/m^2/day
 | (N = 198) | (N = 201) | (N = 198) | (N = 201)
Number of TTP events | 82 | 102 | 121 | 126
Median TTP, weeks | 27.1 | 18.6 | 23.9 | 18.3
(25th, 75th, Percentile), weeks | (17.4, 49.4) | (9.1, 36.9) | (12.0, 44.0) | (6.9, 35.7)
Hazard Ratio (HR) | 0.57 |  | 0.72
(95% CI) | (0.43, 0.77) |  | (0.56, 0.92)
P-value | 0.00013 |  | 0.00762
Response Rate (%) | 23.7 | 13.9 | 31.8 | 17.4
(95% CI) | (18.0, 30.3) | (9.5, 19.5) | (25.4, 38.8) | (12.4, 23.4)
Abbreviations: CI, confidence interval; TTP, time to progression.
aThe time from last tumor assessment to the data cut-off date was greater than 100 days in approximately 30% of patients in the independent assessment. The pre-specified assessment interval was 42 or 84 days.

Figure 1. Kaplan-Meier Estimates for Independent Review Panel-evaluated Time to Progression

Figure 2. Kaplan-Meier Estimates for Investigator Assessment Time to Progression

At the time of above efficacy analysis, the overall survival (OS) data were not mature (32% events). However, based on the TTP results, the study was unblinded and patients receiving capecitabine alone were allowed to cross over to treatment with TYKERB plus capecitabine. The survival data were followed for an additional 2 years to be mature and the analysis is summarized in Table 7.

Table 7. Overall Survival Data
 | TYKERB 1,250 mg/day + Capecitabine 2,000 mg/m^2/day; (N = 207) | Capecitabine 2,500 mg/m^2/day; (N = 201)
Overall Survival
Died | 76% | 82%
Median overall survival (weeks) | 75.0 | 65.9
Hazard ratio, 95% CI; (P-value) | 0.89 (0.71, 1.10); 0.276
Abbreviation: CI, confidence interval.

Clinical Studies Describing Limitations of Use: In two randomized trials, TYKERB-based chemotherapy regimens have been shown to be less effective than trastuzumab-based chemotherapy regimens. The first randomized, open-label study compared the safety and efficacy of TYKERB in combination with capecitabine relative to trastuzumab in combination with capecitabine in women with HER2-positive metastatic breast cancer (N = 540). The study was stopped early based on the findings of a pre-planned interim analysis showing a low incidence of CNS events (primary endpoint) and superior efficacy of the trastuzumab plus capecitabine. The median progression-free survival was 6.6 months in the group receiving TYKERB in combination with capecitabine compared with 8.0 months in the group receiving the trastuzumab combination [HR = 1.30 (95% CI: 1.04, 1.64)]. Overall survival was analyzed when 26% of deaths occurred in the group receiving TYKERB in combination with capecitabine and 22% in the group receiving the trastuzumab combination [HR = 1.34 (95% CI: 0.95, 1.92)].

The second randomized, open-label study compared the safety and efficacy of taxane-based chemotherapy plus TYKERB to taxane-based chemotherapy plus trastuzumab as first-line therapy in women with HER2-positive, metastatic breast cancer (N = 652). The study was stopped early based on findings from a pre-planned interim analysis. The median progression-free survival was 11.3 months in the trastuzumab combination treatment arm compared to 9.0 months in patients treated with TYKERB in the combination arm for the intent-to-treat population [HR = 1.37 (95% CI: 1.13, 1.65)].

14.2 Hormone Receptor-Positive, HER2-Positive Metastatic Breast Cancer

The efficacy and safety of TYKERB in combination with letrozole were evaluated in a double-blind, placebo-controlled, multi-center study. A total of 1286 postmenopausal women with hormone receptor-positive (ER positive and/or PgR positive) metastatic breast cancer, who had not received prior therapy for metastatic disease, were randomly assigned to receive either TYKERB (1,500 mg once daily) plus letrozole (2.5 mg once daily) (n = 642) or letrozole (2.5 mg once daily) alone (n = 644). Of all patients randomized to treatment, 219 (17%) patients had tumors overexpressing the HER2 receptor, defined as fluorescence in situ hybridization (FISH) greater than or equal to 2 or 3+ immunohistochemistry (IHC). There were 952 (74%) patients who were HER2-negative and 115 (9%) patients did not have their HER2 receptor status confirmed. The primary objective was to evaluate and compare progression-free survival (PFS) in the HER2-positive population. Progression-free survival was defined as the interval of time between date of randomization and the earlier date of first documented sign of disease progression or death due to any cause.

The baseline demographic and disease characteristics were balanced between the two treatment arms. The median age was 63 years and 45% were 65 years of age or older. Eighty-four percent (84%) of the patients were white. Approximately 50% of the HER2-positive population had prior adjuvant/neo-adjuvant chemotherapy and 56% had prior hormonal therapy. Only 2 patients had prior trastuzumab.

In the HER2-positive subgroup (n = 219), the addition of TYKERB to letrozole resulted in an improvement in PFS. In the HER2-negative subgroup, there was no improvement in PFS of the combination of TYKERB plus letrozole compared to the letrozole plus placebo. Overall response rate (ORR) was also improved with the combination of TYKERB plus letrozole. The OS data were not mature. Efficacy analyses for the hormone receptor-positive, HER2-positive and HER2-negative subgroups are presented in Table 8 and Figure 3.

Table 8. Efficacy Results
 | HER2-Positive Population |  | HER2-Negative Population
 | TYKERB 1,500 mg/day + Letrozole 2.5 mg/day | Letrozole 2.5 mg/day | TYKERB 1,500 mg/day + Letrozole 2.5 mg/day | Letrozole 2.5 mg/day
 | (N = 111) | (N = 108) | (N = 478) | (N = 474)
Median PFSa, weeks; (95% CI) | 35.4; (24.1, 39.4) | 13.0; (12.0, 23.7) | 59.7; (48.6, 69.7) | 58.3; (47.9, 62.0)
Hazard Ratio (95% CI); P-value | 0.71 (0.53, 0.96); 0.019 |  | 0.90 (0.77, 1.05); 0.188
Response Rate (%); (95% CI) | 27.9; (19.8, 37.2) | 14.8; (8.7, 22.9) | 32.6; (28.4, 37.0) | 31.6; (27.5, 36.0)
Abbreviations: CI, confidence interval; PFS, progression-free survival.
aKaplan-Meier estimate.

Figure 3. Kaplan-Meier Estimates for Progression-Free Survival for the HER2-Positive Population

The efficacy and safety of TYKERB, in combination with an aromatase inhibitor (AI), were confirmed in another randomized Phase 3 trial. Patients enrolled were post-menopausal women who had hormone receptor-positive (HR+)/HER2-positive, metastatic breast cancer, which had progressed after prior trastuzumab-containing chemotherapy and endocrine therapies. A total of 355 patients were randomized in a 1:1:1 ratio to TYKERB 1000 mg + trastuzumab + AI (N = 120), or trastuzumab + AI arm (N = 117), or TYKERB 1500 mg + AI (N = 118). In the trastuzumab-containing arms, trastuzumab was administered with a loading dose of 8 mg/kg IV followed by the maintenance dose of 6 mg/kg every 3 weeks. In the AI-containing arms, the AIs were administered at doses of letrozole 2.5 mg once daily, or exemestane 25 mg once daily, or anastrozole 1 mg once daily.

The study was designed to evaluate a potential benefit in Progression Free Survival (PFS) when double versus single HER2 targeted therapy was administered in combination with an AI (letrozole, exemestane, or anastrozole). The major efficacy outcome measure was PFS based on local radiology/investigator’s assessment comparing TYKERB + trastuzumab + AI versus trastuzumab + AI.

The median age was 56 years (range 30 to 84). The majority of the patients treated on this trial (70%) were Caucasian.

Efficacy results are presented in Table 9 and Figure 4. The OS data were not mature (23% of patients had died).

Table 9. Efficacy Results
 | TYKERB (1,000 mg) + Trastuzumab + AI | Trastuzumab + AI | TYKERB (1,500 mg) + AI
 | (N = 120) | (N = 117) | (N = 118)
Median PFSa, months (95% CI) | 11.0 (8.3, 13.8) | 5.6 (5.4, 8.3) | 8.3 (5.8, 11.1)
Hazard Ratio (95% CI) P-valueb | 0.62 (0.45, 0.88) 0.0040 |  | ---
 | --- | 0.85 (0.62, 1.17) 0.2921c
Response Rate (%)d (95% CI) | 22.5 (15.4, 31.0) | 8.5 (4.2, 15.2) | 12.7 (7.3, 20.1)
Abbreviations: CI, confidence interval; PFS, progression-free survival.
a Kaplan-Meier estimate.
b Stratified log-rank test.
c Nominal p-value. No multiplicity adjustment.
d Confirmed CR + PR; subjects with unknown or missing response were treated as non-responders.

Figure 4. Kaplan-Meier Estimates for Progression-Free Survival

16 HOW SUPPLIED/STORAGE AND HANDLING

The 250 mg tablets of TYKERB are oval, biconvex, orange, and film-coated with ‘GS XJG’ debossed on one side and are available in:

Bottles of 150 tablets: NDC 0078-0671-19

Store at 20°C to 25°C (68°F to 77°F); excursions permitted between 15°C and 30°C (59°F and 86°F) [see USP Controlled Room Temperature].

17 PATIENT COUNSELING INFORMATION

Advise the patient to read the FDA-approved patient labeling (Patient Information).

Inform patients of the following:

Decreased Left Ventricular Ejection Fraction (LVEF)

- TYKERB has been reported to decrease left ventricular ejection fraction which may result in shortness of breath, palpitations, and/or fatigue [see Warnings and Precautions (5.1)]. Advise patients to inform their healthcare provider if they develop these symptoms while taking TYKERB.

Hepatotoxicity and Hepatic Impairment

- Periodic laboratory testing will be performed while taking TYKERB. Advise patients to report signs and symptoms of liver dysfunction to their healthcare provider right away [see Warnings and Precautions (5.2)].

Diarrhea

- TYKERB often causes diarrhea which may be severe in some cases [see Warnings and Precautions (5.4)]. Instruct patients on how to manage and/or prevent diarrhea and to inform their healthcare provider immediately if there is any change in bowel patterns or severe diarrhea occurs during treatment with TYKERB.

Interstitial Lung Disease/Pneumonitis

- Advise patients to report pulmonary signs or symptoms indicative of ILD or pneumonitis [see Warnings and Precautions (5.5)]

Severe Cutaneous Reactions

- Advise patients to report severe cutaneous reactions to their healthcare provider if they develop these symptoms while taking TYKERB [see Warnings and Precautions (5.7)].

Drug and Food Interactions

- TYKERB may interact with many drugs; therefore, advise patients to report to their healthcare provider the use of any other prescription or nonprescription medication or herbal products [see Drug Interactions (7)].
- TYKERB may interact with grapefruit. Advise patients not to take TYKERB with grapefruit products [see Dosage and Administration (2.2) and Drug Interactions (7.2)].

Dosing Administration

- TYKERB should be taken at least one hour before or one hour after a meal, in contrast to capecitabine which should be taken with food or within 30 minutes after food. The dose of TYKERB should be taken once daily. Dividing the daily dose is not recommended [see Dosage and Administration (2.1)].

Embryo-Fetal Toxicity

- Inform female patients of the risk to a fetus and potential loss of the pregnancy. Advise females to inform their healthcare provider if they are pregnant or become pregnant [see Use in Specific Populations (8.1)].
- Advise females of reproductive potential to use effective contraception during treatment with TYKERB and for 1 week after the last dose.
- Advise male patients with female partners of reproductive potential to use effective contraception during treatment and for 1 week following the last dose [see Warning and Precautions (5.8) and Use in Specific Populations (8.1, 8.3)].

Lactation

- Advise patients not to breastfeed during treatment and for 1 week after the last dose of TYKERB [see Use in Specific Populations (8.2)].

Distributed by
Novartis Pharmaceuticals Corporation
East Hanover, New Jersey 07936

© Novartis

T2022-23

PATIENT INFORMATION
TYKERB® (TIE-curb)
(lapatinib)
tablets

What is TYKERB?
TYKERB is a prescription medicine used:

- with the medicine capecitabine to treat people with breast cancer that is advanced or that has spread to other parts of the body (metastatic), and:
  - that is HER2-positive (tumors that produce large amounts of a protein called human epidermal growth factor receptor-2), and
  - who have already had certain other breast cancer treatments
    Before taking TYKERB with capecitabine, your breast cancer should have gotten worse (progressed) with the medicine trastuzumab.
- with the medicine letrozole to treat women who:
  - have gone through the change of life (postmenopausal), and
  - who have metastatic breast cancer that is hormone receptor-positive, HER2-positive, and hormonal therapy is a treatment option for them.

It is not known if TYKERB is safe and effective in children.

Do not take TYKERB if you are allergic to any of the ingredients in TYKERB. A complete list of ingredients in TYKERB can be found at the end of this Patient Information.

Before taking TYKERB, tell your healthcare provider about all of your medical conditions, including if you:

- have heart problems
- have liver problems. You may need a lower dose of TYKERB.

For females, tell your healthcare provider if you:

- are pregnant or plan to become pregnant. TYKERB can harm your unborn baby. Your healthcare provider should check to see if you are pregnant before you start taking TYKERB. You should use effective birth control (contraception) during treatment with TYKERB and for 1 week after the last dose of TYKERB. Tell your healthcare provider right away if you become pregnant during treatment with TYKERB.
- are breastfeeding or plan to breastfeed. It is not known if TYKERB passes into your breast milk. You should not breastfeed during treatment with TYKERB and for 1 week after the last dose of TYKERB. Talk to your healthcare provider about the best way to feed your baby if you breastfeed.

For males with female partners who are able to become pregnant:

- use effective contraception during treatment with TYKERB and for 1 week after the last dose.
- if your female partner becomes pregnant during treatment with TYKERB, tell your healthcare provider right away.

Tell your healthcare provider about all the medicines you take, including prescription and over-the-counter medicines, vitamins, and herbal supplements. TYKERB may affect the way other medicines work, and other medicines may affect the way TYKERB works.

Know the medicines you take. Keep a list of your medicines with you to show your healthcare provider and pharmacist when you get a new medicine. Do not take other medicines during treatment with TYKERB without first talking with your healthcare provider.

How should I take TYKERB?

- Take TYKERB exactly as your healthcare provider tells you to take it. Your healthcare provider may change your dose of TYKERB if needed.
- For people with advanced or metastatic breast cancer, TYKERB and capecitabine are taken in 21-day cycles. The usual dose of TYKERB is 1,250 mg (5 tablets) taken by mouth all at the same time, 1 time a day on Days 1 to 21.
- Your healthcare provider will tell you the dose of capecitabine you should take and when you should take it.
- Take capecitabine with food or within 30 minutes after food.
- For people with hormone receptor-positive, HER2-positive breast cancer, TYKERB and letrozole are taken every day. The usual dose of TYKERB is 1,500 mg (6 tablets) taken by mouth all at the same time, 1 time a day. Your healthcare provider will tell you the dose of letrozole you should take and when you should take it.
- Take TYKERB at least 1 hour before, or at least 1 hour after a meal.
- Avoid eating or drinking grapefruit products during treatment with TYKERB.
- If you miss a dose of TYKERB, take your next dose at your regular time the next day.
- If you take too much TYKERB, call your healthcare provider or go to the nearest hospital emergency room right away.

What are the possible side effects of TYKERB?
TYKERB may cause serious side effects, including:

- heart problems, including decreased pumping of blood from the heart and an abnormal heartbeat. Signs and symptoms of an abnormal heartbeat include:

- feeling like your heart is pounding or racing
- dizziness
- tiredness

- feeling lightheaded
- shortness of breath

Your healthcare provider should check your heart function before you start taking TYKERB and during treatment.

- liver problems. Liver problems can be severe and deaths have happened. Signs and symptoms of liver problems include:
  - itching
  - yellowing of your skin or the white part of your eyes
  - dark urine
  - pain or discomfort in the right upper stomach area

Your healthcare provider should do blood tests to check your liver before you start taking TYKERB and during treatment.

- diarrhea. Diarrhea is common with TYKERB and may sometimes be severe. Severe diarrhea can cause loss of body fluid (dehydration) and some deaths have happened. Call your healthcare provider right away if you have a change in bowel pattern or if you have severe diarrhea. Follow your healthcare provider’s instructions for what to do to help prevent or treat diarrhea.
- lung problems. Symptoms of a lung problem with TYKERB include a cough that will not go away or shortness of breath.
- severe skin reactions. TYKERB may cause severe skin reactions. Tell your healthcare provider right away if you develop a skin rash, red skin, blistering of the lips, eyes, or mouth, peeling of the skin, fever, or any combination of these. As severe skin reactions can be life-threatening, your healthcare provider may tell you to stop taking TYKERB.

Call your healthcare provider right away if you have any of the signs or symptoms of the serious side effects listed above.

Common side effects of TYKERB in combination with capecitabine or letrozole include:

- diarrhea
- red, painful hands and feet
- nausea
- rash
- vomiting
- inflamed mouth, digestive tract and airways
- mouth sores
- headache
- unusual hair loss or thinning
- shortness of breath

- dry skin
- itching
- tiredness
- painful arms, legs and back
- loss of appetite
- indigestion
- nose bleeds
- nail disorders, such as nail bed changes, nail pain, infection and swelling of the cuticles
- difficulty sleeping

Tell your healthcare provider if you have any side effect that bothers you or that does not go away.

These are not all the possible side effects of TYKERB. For more information, ask your healthcare provider or pharmacist.

Call your healthcare provider for medical advice about side effects. You may report side effects to FDA at 1-800-FDA-1088.

You may also get side effects from the other medicines taken with TYKERB. Talk to your healthcare provider about possible side effects you may get during treatment.

How should I store TYKERB?

- Store TYKERB at room temperature between 68°F to 77°F (20°C to 25°C).
- Do not keep medicine that is out of date or that you no longer need.

Keep TYKERB and all medicines out of the reach of children.

General information about the safe and effective use of TYKERB.
Medicines are sometimes prescribed for purposes other than those listed in a Patient Information leaflet. Do not use TYKERB for a condition for which it was not prescribed. Do not give TYKERB to other people, even if they have the same symptoms that you have. It may harm them. You can ask your pharmacist or healthcare provider for information about TYKERB that is written for health professionals.

What are the ingredients in TYKERB?
Active ingredient: Lapatinib.
Inactive ingredients: Tablet Core: Magnesium stearate, microcrystalline cellulose, povidone, sodium starch glycolate. Coating: Orange film-coat: FD&C yellow No. 6/sunset yellow FCF aluminum lake, hypromellose, macrogol/PEG 400, polysorbate 80, titanium dioxide.
Distributed by: Novartis Pharmaceuticals Corporation, East Hanover, New Jersey 07936
© Novartis
For more information, call 1-888-669-6682.

This Patient Information has been approved by the U.S. Food and Drug Administration.

Revised: December 2024

T2024-87

PRINCIPAL DISPLAY PANEL

NDC 0078-0671-19

NOVARTIS

Tykerb®
(lapatinib) Tablets

250 mg

150 Tablets

Rx only